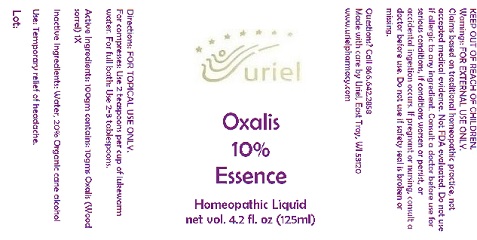 DRUG LABEL: Oxalis 10% Essence
NDC: 48951-7160 | Form: LIQUID
Manufacturer: Uriel Pharmacy Inc.
Category: homeopathic | Type: HUMAN OTC DRUG LABEL
Date: 20180508

ACTIVE INGREDIENTS: OXALIS STRICTA WHOLE 1 [hp_X]/1 mL
INACTIVE INGREDIENTS: ALCOHOL; WATER

Oxalis 10% Essence

INDICATIONS AND USAGE

Directions: FOR TOPICAL USE ONLY.

DOSAGE AND ADMINISTRATION

For compresses: Use 2 teaspoons per cup of lukewarm water. For full bath: Use 2-3 tablespoons.

ACTIVE INGREDIENT

Active Ingredients: 100gm contains: 10gms Oxalis (Wood sorrel) 1X

Inactive Ingredients: Water, 20% Organic cane alcohol

PURPOSE

Use: Temporary relief of headache.

KEEP OUT OF REACH OF CHILDREN.

Warnings: FOR EXTERNAL USE ONLY.
Claims based on traditional homeopathic practice, not accepted medical evidence. Not FDA evaluated. Do not use if allergic to any ingredient. Consult a doctor before use for serious conditions, if conditions worsen or persist, or accidental ingestion occurs. If pregnant or nursing, consult a doctor before use. Do not use if safety seal is broken or missing.

Questions? Call 866.642.2858
Made with care by Uriel, East Troy, WI 53120
www.urielpharmacy.com